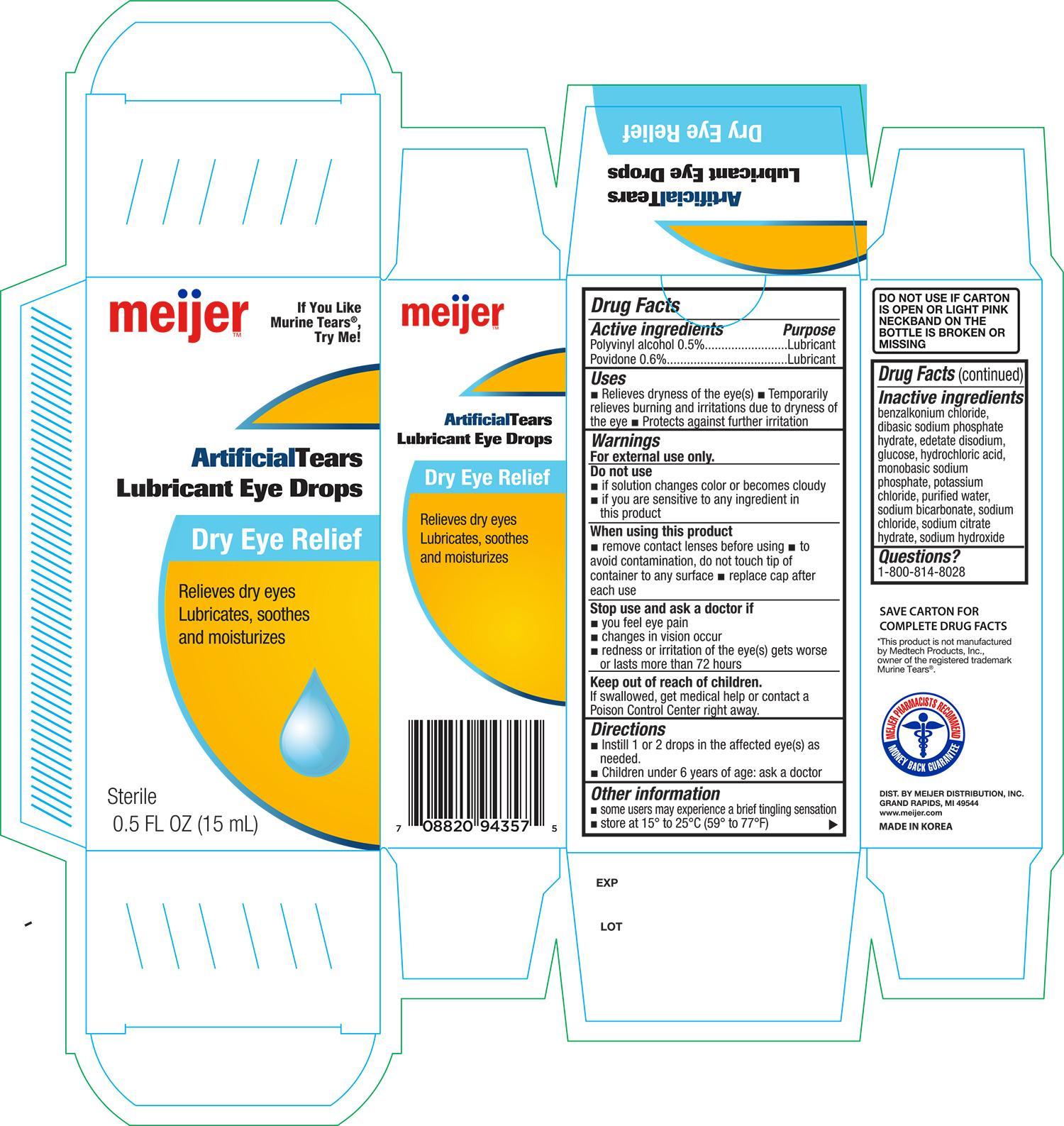 DRUG LABEL: Meijer Artificial Tears Lubricant Eye
NDC: 41250-357 | Form: SOLUTION/ DROPS
Manufacturer: Meijer, Inc.
Category: otc | Type: HUMAN OTC DRUG LABEL
Date: 20141229

ACTIVE INGREDIENTS: POLYVINYL ALCOHOL 5 mg/1 mL; POVIDONE 6 mg/1 mL
INACTIVE INGREDIENTS: BENZALKONIUM CHLORIDE; SODIUM PHOSPHATE, DIBASIC, DIHYDRATE; EDETATE DISODIUM; HYDROCHLORIC ACID; SODIUM PHOSPHATE, MONOBASIC; POTASSIUM CHLORIDE; WATER; SODIUM BICARBONATE; SODIUM CHLORIDE; SODIUM HYDROXIDE

Active ingredients Purpose

Polyvinyl alcohol 0.5%...................................................... Lubricant

Povidone 0.6%................................................................. Lubricant

Uses

- Relieves dryness of the eye(s)
- Temporarily relieves burning and irritations due to dryness of the eye
- Protects against further irritation

Warnings

For external use only

Do not use

- if solution changes color or becomes cloudy
- if you are sensitive to any ingredient in this product

When using this product

- remove contact lenses before using
- to avoid contamination, do not touch tip of container to any surface
- replace cap after each use

Stop use and ask a doctor if

- you feel eye pain
- changes in vision occur
- redness or irritation of the eye(s) gets worse or lasts more than 72 hours

Keep out of reach of children

If swallowed, get medical help or contact a Poison Control Center right away

Directions

- Instill 1 or 2 drops in the affected eye(s) as needed
- Children under 6 years of age: ask a doctor

Other information

- some users may experience a brief tingling sensation
- store at 15° to 25°C (59° to 77°F)

INACTIVE INGREDIENT

benzlkonium chloride, dibasic sodium phosphate hydrate, edetate disodium, glucose, hydrochlorid acid, monobasic sodium phosphate, potassium chloride, purified water, sodium bicarbonate, sodium chloride, sodium citrate hydrate, sodium hydroxide

DOSAGE AND ADMINISTRATION

DISTRIBUTED BY:

MEIJER DISTRIBUTION, INC.

GRAND RAPIDS, MI 49544

WWW.MEIJER.COM

MADE IN KOREA